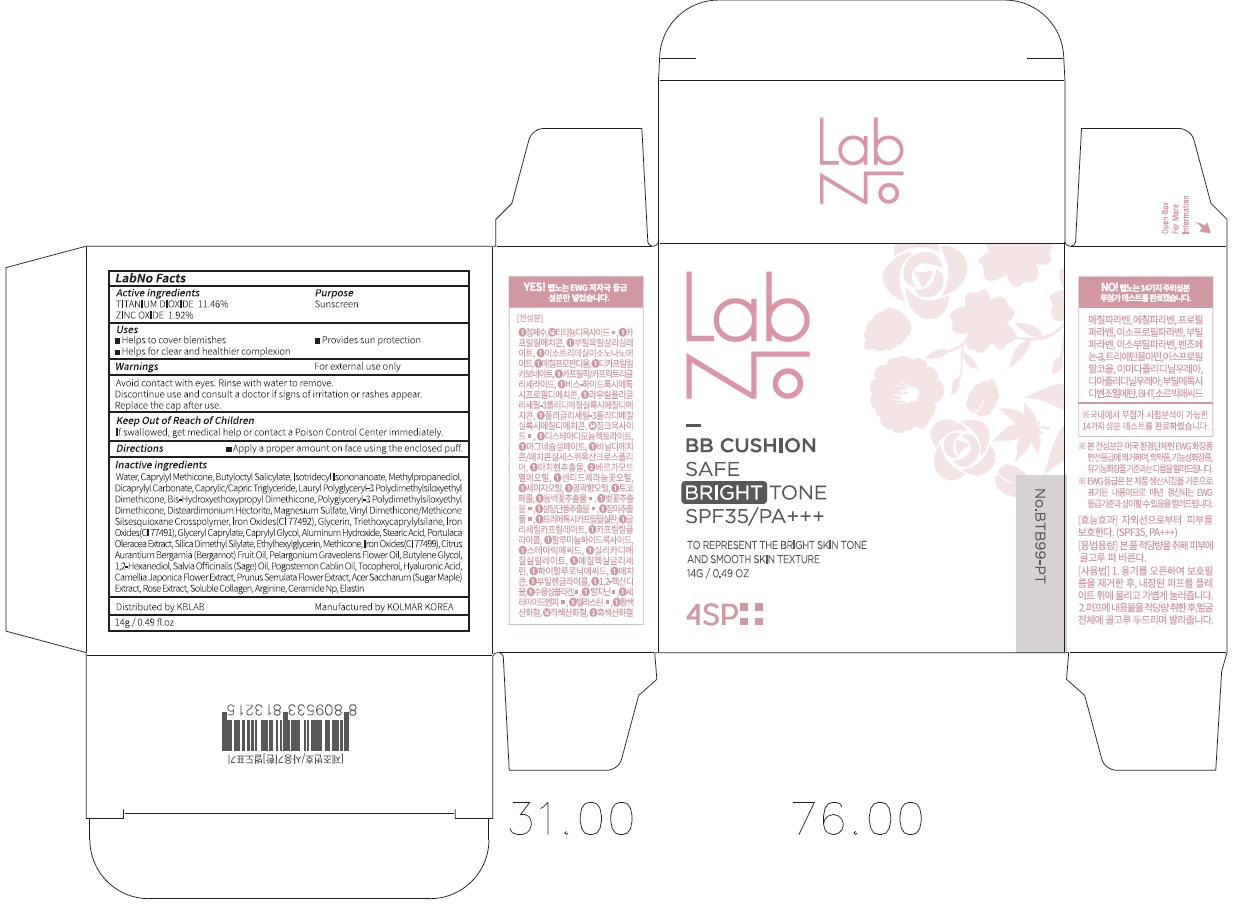 DRUG LABEL: LabNo 4SP Safe Bright Tone BB Cushion
NDC: 71497-030 | Form: POWDER
Manufacturer: KB Lab Co., Ltd.
Category: otc | Type: HUMAN OTC DRUG LABEL
Date: 20170714

ACTIVE INGREDIENTS: Titanium Dioxide 1.60 g/14 g; ZINC OXIDE 0.26 g/14 g
INACTIVE INGREDIENTS: Water; Butyloctyl Salicylate

ACTIVE INGREDIENT

Active ingredients: TITANIUM DIOXIDE 11.46%, ZINC OXIDE 1.92%

INACTIVE INGREDIENT

Inactive ingredients: Water, Caprylyl Methicone, Butyloctyl Salicylate, Isotridecyl Isononanoate, Methylpropanediol, Dicaprylyl Carbonate, Caprylic/Capric Triglyceride, Lauryl Polyglyceryl-3 Polydimethylsiloxyethyl Dimethicone, Bis-Hydroxyethoxypropyl Dimethicone, Polyglyceryl-3 Polydimethylsiloxyethyl Dimethicone, Disteardimonium Hectorite, Magnesium Sulfate, Vinyl Dimethicone/Methicone Silsesquioxane Crosspolymer, Iron Oxides(CI 77492), Glycerin, Triethoxycaprylylsilane, Iron Oxides(CI 77491), Glyceryl Caprylate, Caprylyl Glycol, Aluminum Hydroxide, Stearic Acid, Portulaca Oleracea Extract, Silica Dimethyl Silylate, Ethylhexylglycerin, Methicone, Iron Oxides(CI 77499), Citrus Aurantium Bergamia (Bergamot) Fruit Oil, Pelargonium Graveolens Flower Oil, Butylene Glycol, 1,2-Hexanediol, Salvia Officinalis (Sage) Oil, Pogostemon Cablin Oil, Tocopherol, Hyaluronic Acid, Camellia Japonica Flower Extract, Prunus Serrulata Flower Extract, Acer Saccharum (Sugar Maple) Extract, Rose Extract, Soluble Collagen, Arginine, Ceramide Np, Elastin

PURPOSE

Purpose: Sunscreen

WARNINGS

Warnings: For external use only Avoid contact with eyes. Rinse with water to remove. Discontinue use and consult a doctor if signs of irritation or rashes appear. Replace the cap after use.

Keep Out of Reach of Children If swallowed, get medical help or contact a Poison Control Center immediately.

DESCRIPTION

Uses:

- Helps to cover blemishes

- Helps for clear and healthier complexion

- Provides sun protection

Directions:

Apply a proper amount on face using the enclosed puff.